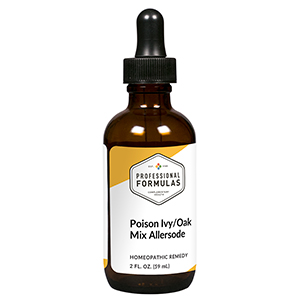 DRUG LABEL: Poison Ivy/Oak
NDC: 63083-1013 | Form: LIQUID
Manufacturer: Professional Complementary Health Formulas
Category: homeopathic | Type: HUMAN OTC DRUG LABEL
Date: 20190815

ACTIVE INGREDIENTS: ECHINACEA PURPUREA WHOLE 2 [hp_X]/59 mL; SUS SCROFA ADRENAL GLAND 6 [hp_X]/59 mL; CORTICOTROPIN 6 [hp_X]/59 mL; BEEF LIVER 6 [hp_X]/59 mL; CROTON TIGLIUM SEED 8 [hp_X]/59 mL; HISTAMINE DIHYDROCHLORIDE 12 [hp_X]/59 mL; WOOD CREOSOTE 12 [hp_X]/59 mL; XEROPHYLLUM ASPHODELOIDES WHOLE 12 [hp_X]/59 mL; TOXICODENDRON DIVERSILOBUM LEAF 6 [hp_X]/59 mL; TOXICODENDRON PUBESCENS LEAF 6 [hp_X]/59 mL; URTICA DIOICA SUBSP. DIOICA LEAF 6 [hp_X]/59 mL; AILANTHUS ALTISSIMA FRUIT 6 [hp_X]/59 mL
INACTIVE INGREDIENTS: ALCOHOL; WATER

AOAK

ACTIVE INGREDIENTS

Echinacea purpurea 2X
Adrenal 6X
ACTH 6X, 30X
Liver 6X, 12X
Croton tiglium 8X
Histaminum hydrochloricum 12X
Kreosotum 12X
Xerophyllum 12X
and all the following at 6X, 12X, 60X, 100X:
Rhus diversiloba (poison oak)
Rhus toxicodendron (poison ivy)
Stinging nettle
Sumac

QUESTIONS

Professional Formulas

PO Box 2034 Lake Oswego, OR 97035

INDICATIONS

For the temporary relief of redness, swelling, stinging, itching of skin, and itching of nose or throat due to sensitivity to poison ivy and poison oak.*

PURPOSE

*Claims based on traditional homeopathic practice, not accepted medical evidence. Not FDA evaluated.

WARNINGS

Severe symptoms such as difficulty breathing, facial swelling, dizziness, confusion, and hives may be life-threatening and require immediate emergency care. Keep out of the reach of children. In case of overdose, get medical help or contact a poison control center right away. If pregnant or breastfeeding, ask a healthcare professional before use.

Keep out of the reach of children.

PREGNANCY OR BREAST FEEDING

If pregnant or breastfeeding, ask a healthcare professional before use.

DIRECTIONS

Place drops under tongue 30 minutes before/after meals. Adults and children 12 years and over: Take 10 to 15 drops up to 3 times per day. For desensitization, begin with 1 to 5 drops daily, increasing to the standard dose gradually to avoid symptom expression; after 1 to 3 months at the standard dose, decrease gradually to a maintenance dose of 10 to 15 drops weekly. Consult a physician for use in children under 12 years of age.

OTHER INFORMATION

Tamper resistant. If seal is broken, do not use. After opening, close container tightly and store at room temperature away from heat.

INACTIVE INGREDIENTS

20% ethanol, purified water.

LABEL

Est 1985

Professional Formulas

Complementary Health

Poison Ivy/Oak

Homeopathic Remedy

2 FL. OZ. (59 mL)